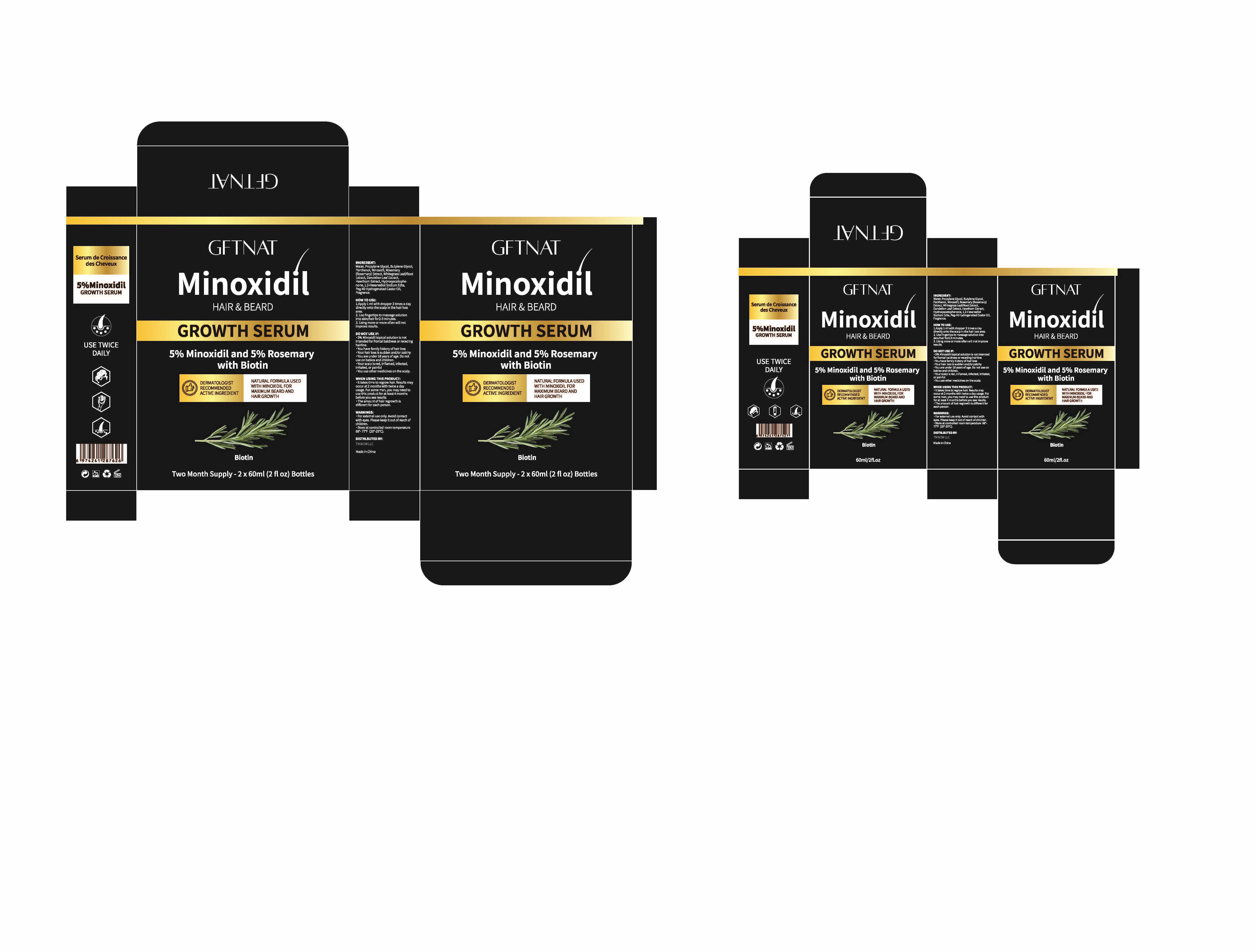 DRUG LABEL: 5% Minoxidil and 5% Rosemary for Hair Care
NDC: 84454-001 | Form: LIQUID
Manufacturer: TIKNOW LLC
Category: otc | Type: HUMAN OTC DRUG LABEL
Date: 20250707

ACTIVE INGREDIENTS: MINOXIDIL 5 g/100 mL; ROSEMARY 5 g/100 mL
INACTIVE INGREDIENTS: PROPYLENE GLYCOL; WATER; HYDROXYACETOPHENONE; PEG-40 CASTOR OIL; BUTYLENE GLYCOL; PANTHENOL

ACTIVE INGREDIENT

5% Minoxidil.........Hair regrowth treatment

5% Rosemary...........Anti-hair loss

DESCRIPTION

Use: To regrow hair of scalp and beard

HOW TO USE

1. Apply 1ml with dropper 2 times a day directly onto the scalp in the hair loss area.

2. Use fingertips to massage solution into skin/hair for 2-3 minutes.

3. Using more or more often will not improve results.

DOSAGE & ADMINISTRATION

Apply 1 ml with dropper 2 times a day.

DO NOT USE IF:

- 5% Minoxidil topical solution is not intended for frontal baldness or receding hairline.
- You have family history of hair loss.
- Your hair loss is sudden and/or patchy
- You are under 18 yearrs of age.Do not use on babies and children.
- Your scalp is red, inflamed, infected, irritated, or painful
- You use other medicines on the scalp.

WHEN USING THIS PRODUCT:

- It takes time to regrow hair. Results may occur at 2 months with twice a day usage. For some men, you may need to use this product for at least 4 months before you see results.
- The amount of hair regroth is different for each person.

WARNINGS:

- For external use only. Avoild contact with eyes. Please keep it out of reach of children.
- Store at controlled room temperature 66°-77°F (20°-25℃).

KEEP OUT OF REACH OF CHILDREN

INACTIVE INGREDIENT

Water, Propylene Glycol, Butylene Glycol, Panthenol, Whitegrass Leaf/Root Extract, Dandelion Leaf Extract, Hawthorn Extract, Hydroxyacetophenone, 1.2-Hexanediol Sodium Edta, Peg-40 Hydrogenated Castor Oil, Fragrance

PACKAGE LABEL

84454-001-01, 84454-001-02, 84454-001-06